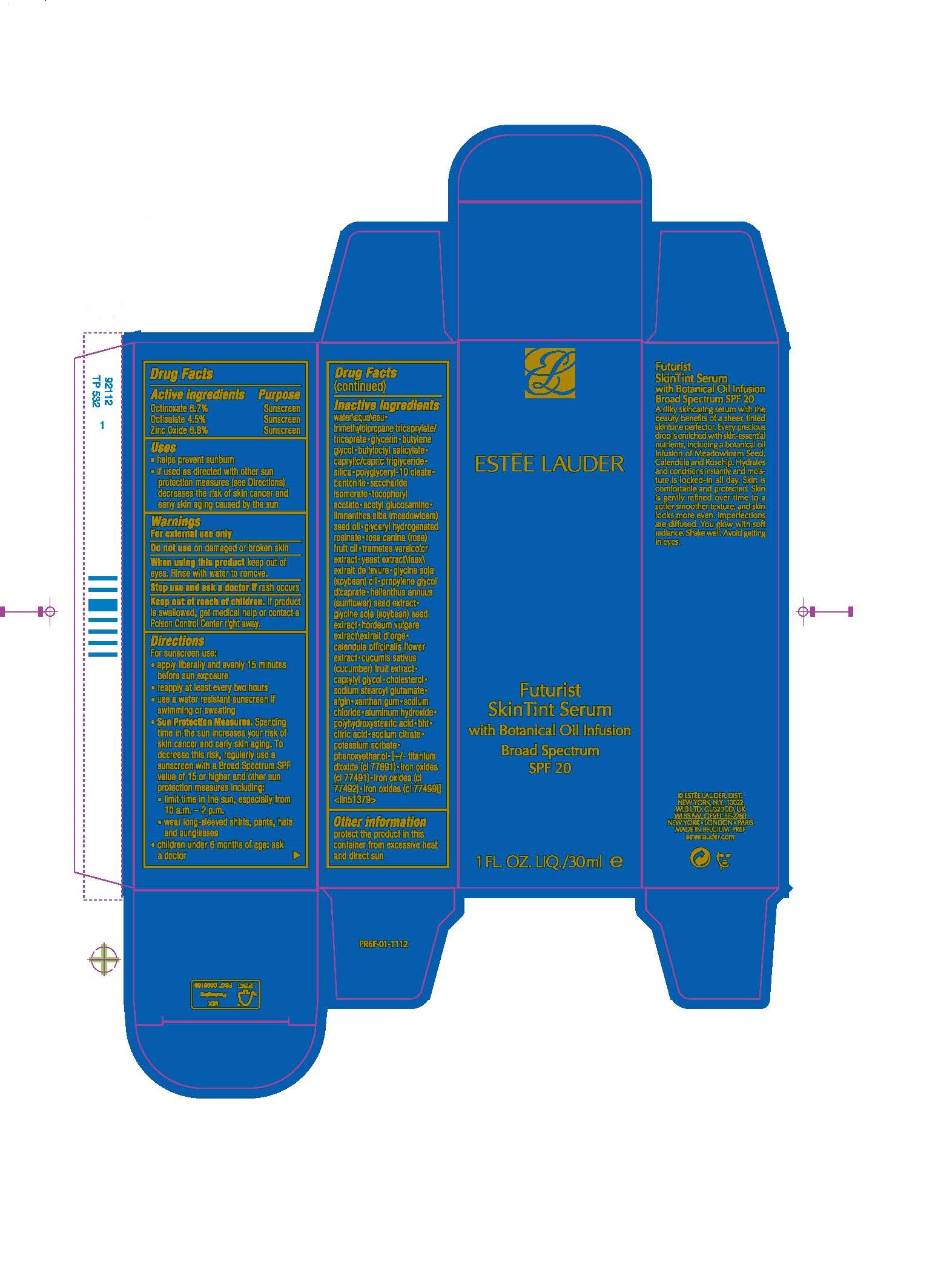 DRUG LABEL: FUTURIST SKIN TINT SERUM
NDC: 11559-063 | Form: CREAM
Manufacturer: ESTEE LAUDER INC
Category: otc | Type: HUMAN OTC DRUG LABEL
Date: 20240813

ACTIVE INGREDIENTS: OCTINOXATE 67 mg/1 mL; ZINC OXIDE 68 mg/1 mL; OCTISALATE 45 mg/1 mL
INACTIVE INGREDIENTS: GLYCERIN; BUTYLENE GLYCOL; WATER; TRIMETHYLOLPROPANE TRICAPRYLATE/TRICAPRATE; GLYCERYL ROSINATE; ROSA CANINA FRUIT; CITRIC ACID MONOHYDRATE; TRAMETES VERSICOLOR FRUITING BODY; SODIUM CHLORIDE; BENTONITE; SODIUM ALGINATE; CALENDULA OFFICINALIS FLOWER; MEDIUM-CHAIN TRIGLYCERIDES; SILICON DIOXIDE; N-ACETYLGLUCOSAMINE; MEADOWFOAM SEED OIL; YEAST, UNSPECIFIED; CUCUMBER; ALUMINUM HYDROXIDE; TITANIUM DIOXIDE; SOYBEAN; HORDEUM VULGARE WHOLE; CAPRYLYL GLYCOL; POLYHYDROXYSTEARIC ACID (2300 MW); PHENOXYETHANOL; BUTYLOCTYL SALICYLATE; SACCHARIDE ISOMERATE; .ALPHA.-TOCOPHEROL ACETATE; SOYBEAN OIL; PROPYLENE GLYCOL DICAPRATE; SUNFLOWER SEED; CHOLESTEROL; SODIUM STEAROYL GLUTAMATE; XANTHAN GUM; BUTYLATED HYDROXYTOLUENE; POLYGLYCERYL-10 OLEATE; SODIUM CITRATE; POTASSIUM SORBATE; FERRIC OXIDE RED; FERRIC OXIDE YELLOW; FERROSOFERRIC OXIDE

FUTURIST SKIN TINT SERUM

Active ingredients

Octinoxate 6.7%
Octisalate 4.5%

Zinc Oxide 6.8%

Purpose

Sunscreen

USE

helps prevent sunburn

WARNINGS

For External Use Only

DO NOT USE

on damaged or broken skin

WHEN USING

keep out of eyes. Rinse with water to remove.

Stop use and ask a doctor if rash occurs

Keep out of reach of children. If product is swallowed, get medical help or contact a Poison Control Center right away.

Directions

Directions For sunscreen use: • apply liberally and evenly 15 minutes before sun exposure • reapply at least every two hours • use a water resistant sunscreen if swimming or sweating • Sun Protection Measures. Spending time in the sun increases your risk of skin cancer and early skin aging. To decrease this risk, regularly use a sunscreen with a Broad Spectrum SPF value of 15 or higher and other sun protection measures including: • limit time in the sun, especially from 10 a.m. – 2 p.m. • wear long-sleeved shirts, pants, hats and sunglasses • children under 6 months of age: ask a doctor

Inactive Ingredients

WATER\AQUA\EAU [] TRIMETHYLOLPROPANE TRICAPRYLATE/TRICAPRATE [] GLYCERIN [] BUTYLENE GLYCOL [] BUTYLOCTYL SALICYLATE [] CAPRYLIC/CAPRIC TRIGLYCERIDE [] SILICA [] POLYGLYCERYL-10 OLEATE [] BENTONITE [] SACCHARIDE ISOMERATE [] TOCOPHERYL ACETATE [] ACETYL GLUCOSAMINE [] LIMNANTHES ALBA (MEADOWFOAM) SEED OIL [] GLYCERYL HYDROGENATED ROSINATE [] ROSA CANINA (ROSE) FRUIT OIL [] TRAMETES VERSICOLOR EXTRACT [] YEAST EXTRACT\FAEX\EXTRAIT DE LEVURE [] GLYCINE SOJA (SOYBEAN) OIL [] PROPYLENE GLYCOL DICAPRATE [] HELIANTHUS ANNUUS (SUNFLOWER) SEED EXTRACT [] GLYCINE SOJA (SOYBEAN) SEED EXTRACT [] HORDEUM VULGARE EXTRACT\EXTRAIT D'ORGE [] CALENDULA OFFICINALIS FLOWER EXTRACT [] CUCUMIS SATIVUS (CUCUMBER) FRUIT EXTRACT [] CAPRYLYL GLYCOL [] CHOLESTEROL [] SODIUM STEAROYL GLUTAMATE [] ALGIN [] XANTHAN GUM [] SODIUM CHLORIDE [] ALUMINUM HYDROXIDE [] POLYHYDROXYSTEARIC ACID [] BHT [] CITRIC ACID [] SODIUM CITRATE [] POTASSIUM SORBATE [] PHENOXYETHANOL [] [+/- TITANIUM DIOXIDE (CI 77891) [] IRON OXIDES (CI 77491) [] IRON OXIDES (CI 77492) [] IRON OXIDES (CI 77499)] <ILN51379>

Other information

protect the product in this container from excessive heat and direct sun

PRINCIPAL DISPLAY PANEL

ESTEE LAUDER
Futurist Skin Tint Serum with Botanical Oil Infusion Broad Spectrum SPF 20

1 FL. OZ. LIQ./30ml